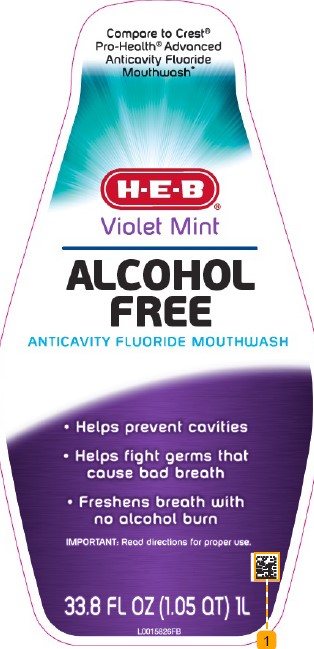 DRUG LABEL: Alcohol-Free Anticavity
NDC: 37808-942 | Form: LIQUID
Manufacturer: H E B
Category: otc | Type: HUMAN OTC DRUG LABEL
Date: 20260224

ACTIVE INGREDIENTS: SODIUM FLUORIDE 0.1 mg/1 mL
INACTIVE INGREDIENTS: WATER; GLYCERIN; CETYLPYRIDINIUM CHLORIDE; CINNAMALDEHYDE; SACCHARIN SODIUM; PHOSPHORIC ACID; SODIUM BENZOATE; SUCRALOSE; POLOXAMER 407; BENZOIC ACID; SODIUM PHOSPHATE, DIBASIC, ANHYDROUS; PROPYLENE GLYCOL; D&C RED NO. 33; FD&C GREEN NO. 3

HEB 482.002/482AC
Alcohol Free Fluoride Violet Mint Mouthwash

TEP

SEALED WITH PRINTED NECKBAND FOR YOUR PROTECTION

H-E-B ®

Violet Mint

ALCOHOL FREE

Active ingredient

Sodium fluoride 0.02%

(0.01% w/v fluoride ion)

Purpose

Anticavity

Use

aids in the prevention of dental cavities

Warnings

for this product

Keep out of reach of children.

If more than used for rinsing is accidentally swallowed, get medical help or contact a Poison Control Center right away.

Directions

Adults and children 6 years of age and older:

- use twice daily after brushing your teeth with a toothpaste
- vigorously swish 10 mL (2 teaspoonfuls) of rinse between your teeth for 1 minute then spit out
- do not swallow the rinse
- do not eat or drink for 30 minutes after rinsing
- instruct children under 12 years of age in good rinsing habits (to minimize swallowing)
- supervise children as necessary until capable of using without supervision
- children under 6 years of age: consult a dentist or doctor

Inactive ingredients

water, glycerin, cetylpyridinium chloride, flavor, cinnamal, sodium saccharin, phosphoric acid, sodium benzoate, sucralose, poloxamer 407, benzoic acid, disodium phosphate, propylene glycol, red 33, green 3

Questions?

Call 1-888-593-0593

Disclaimer

This rinse may cause temporary staining to the surface of teeth. This is not harmful, and adequate brushing may prevent its occurence.

*This product is not manufactured or distributed by Procter & Gamble, distributor of Crest ® Pro-Health ® Advanced Anticavity Fluoride Mouthwash.

MADE WITH PRIDE AND CARE FOR H-E-B ®

SAN ANTONIO, TX, 78204

H-E-B

100% GUARANTEE PROMISE

If you aren't completely pleased with this product, we'll be happy to replace it or refund your money. You have our word on it.

6856-1612

Principal Panel Display

Compare to Crest ® Pro-Health ® Advanced Anticavity Fluoride Mouthwash*

H-E-B ®

Violet Mint

ALCOHOL FREE

ANTICAVITY FLUORIDE MOUTHWASH

- Helps prevent cavities
- Helps fight germs that cause bad breath
- Freshens breath with no alcohol burn

IMPORTANT: Read directions for proper use.

33.8 FL OZ (1.05 QT) 1 L